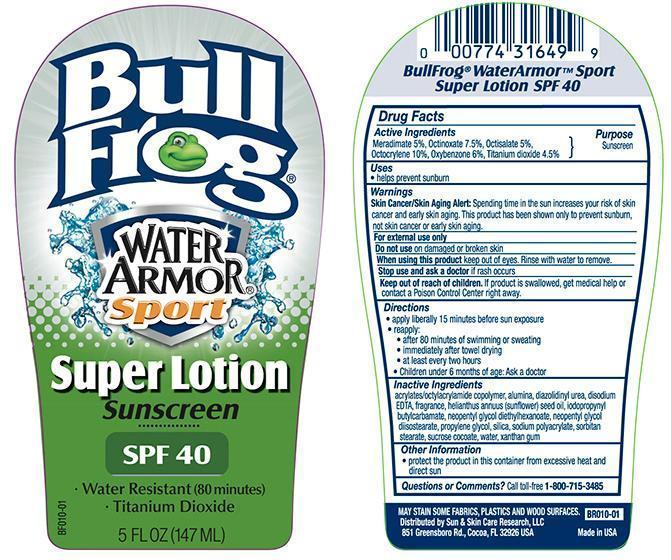 DRUG LABEL: Bull Frog Water Armor Super 40
NDC: 62802-649 | Form: LOTION
Manufacturer: Sun & Skin Care Research, LLC
Category: otc | Type: HUMAN OTC DRUG LABEL
Date: 20140718

ACTIVE INGREDIENTS: MERADIMATE 5 g/100 g; OCTISALATE 5 g/100 g; OCTINOXATE 7.5 g/100 g; OCTOCRYLENE 10 g/100 g; OXYBENZONE 6 g/100 g; TITANIUM DIOXIDE 4.5 g/100 g
INACTIVE INGREDIENTS: WATER; XANTHAN GUM; SUCROSE COCOATE; PEG-40 SORBITAN STEARATE; SODIUM POLYACRYLATE (8000 MW); SILICON DIOXIDE; PROPYLENE GLYCOL; NEOPENTYL GLYCOL DIISOSTEARATE; NEOPENTYL GLYCOL DIETHYLHEXANOATE; IODOPROPYNYL BUTYLCARBAMATE; SUNFLOWER SEED OIL GLYCERETH-8 ESTERS; EDETATE DISODIUM; DIAZOLIDINYL UREA; ALUMINUM OXIDE

Drug Facts

Active Ingredients

- Meradimate: 5%
- Octinoxate: 7.5%
- Octisalate: 5%
- Octocrylene: 10%
- Oxybenzone: 6%
- Titanium Dioxide: 4.5%

Purpose

Sunscreen

Uses

- helps prevent sunburn

Warnings

Skin Cancer/Skin Aging Alert: Spending time in the sun increases your risk of skin cancer and early skin aging. This product has been shown only to prevent sunburn, not skin cancer or early skin aging.

For external use only. Do not use on damaged or broken skin. Stop use and ask a doctor if rash occurs. When using this product keep out of eyes. Rinse with water to remove. Keep out of the reach of children. If swallowed, get medical help or contact a Poison Control Center right away.

Directions

- apply liberally 15 minutes before sun exposure
- reapply after 80 minutes of swimming or sweating
- immediately after towel drying
- at least every 2 hours
- Children under 6 months: Ask a doctor

Other Information

- For use on skin only
- Avoid contact with fabric
- Protect this product from excessive heat and direct sun